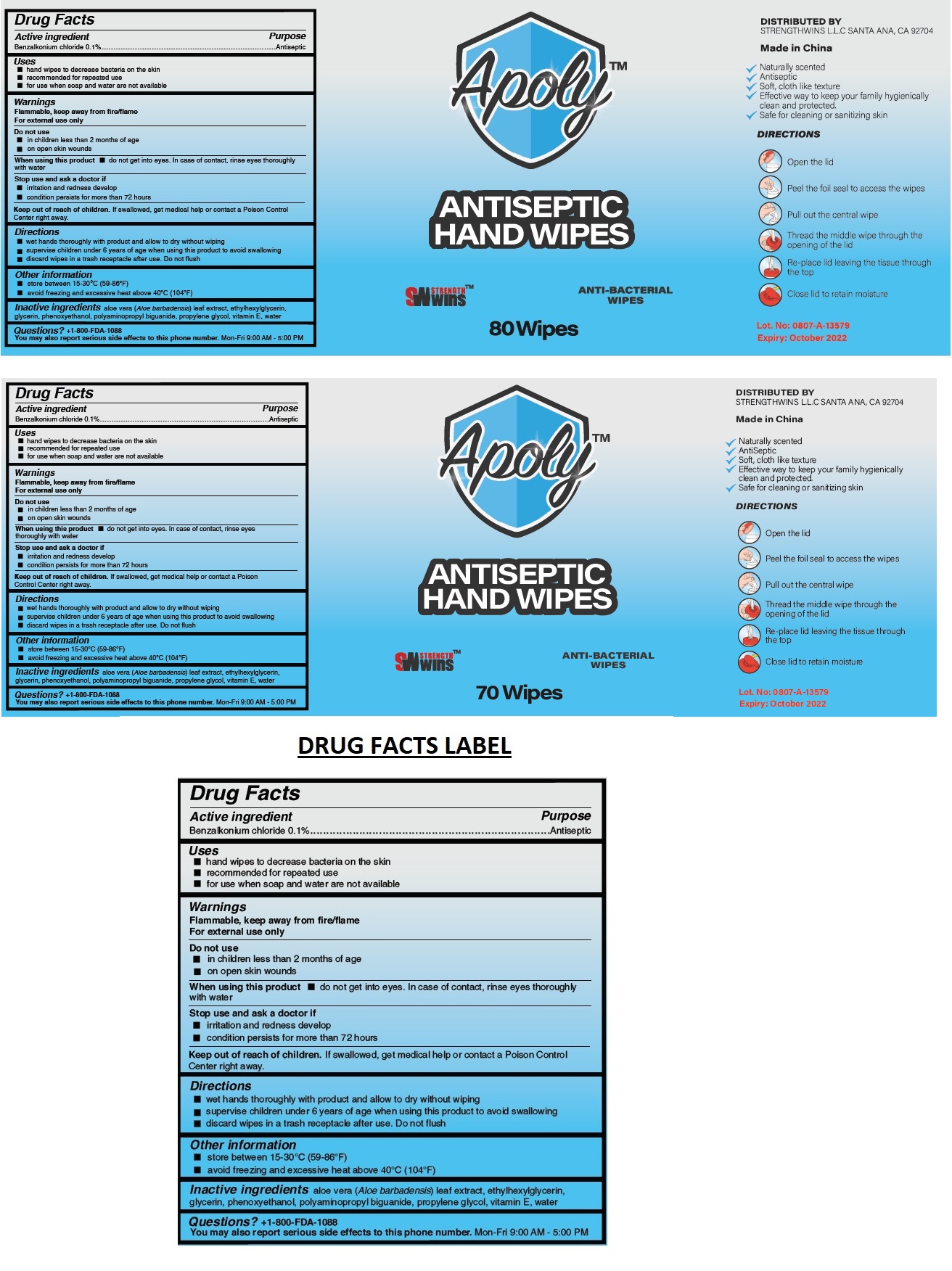 DRUG LABEL: StrengthWins Antiseptic Hand Wipes
NDC: 80698-798 | Form: CLOTH
Manufacturer: Strengthwins
Category: otc | Type: HUMAN OTC DRUG LABEL
Date: 20201202

ACTIVE INGREDIENTS: BENZALKONIUM CHLORIDE 0.1 g/100 mL
INACTIVE INGREDIENTS: ALOE VERA LEAF; ETHYLHEXYLGLYCERIN; GLYCERIN; PHENOXYETHANOL; POLYAMINOPROPYL BIGUANIDE; PROPYLENE GLYCOL; .ALPHA.-TOCOPHEROL; WATER

STRENGTHWINS™ ANTISEPTIC HAND WIPES

Active ingredient

Benzalkonium chloride 0.1%

Purpose

Antiseptic

Uses

• hand wipes to decrease bacteria on the skin

• recommended for repeated use

• for use when soap and water are not available

Warnings

Flammable, keep away from fire/flame
For external use only

Do not use

• in children less than 2 months of age
• on open skin wounds

When using this product • do not get into eyes. In case of contact, rinse eyes thoroughly with water

Stop use and ask a doctor if
• irritation and redness develop

• condition persists for more than 72 hours

Keep out of reach of children. If swallowed, get medical help or contact a Poison Control Center right away.

Directions

• wet hands thoroughly with product and allow to dry without wiping

• supervise children under 6 years of age when using this product to avoid swallowing

• discard wipes in a trash receptacle after use. Do not flush

Other information

• store between 15-30°C (59-86°F)
• avoid freezing and excessive heat above 40°C (104°F)

INACTIVE INGREDIENT

Inactive ingredients aloe vera (Aloe barbadensis) leaf extract, ethylhexylglycerin, glycerin, phenoxyethanol, polyaminopropyl biguanide, propylene glycol, vitamin E, water

Questions? +1-800-FDA-1088
You may also report serious side effects to this phone number. Mon-Fri 9:00 AM - 5:00 PM

Apoly™

ANTI-BACTERIAL WIPES

DISTRIBUTED BY

STRENGTHWINS L.L.C SANTA ANA, CA 92704

Made in China

• Naturally scented

• Antiseptic

• Soft, cloth like texture

• Effective way to keep your family hygienically clean and protected.

• Safe for cleaning or sanitizing skin

DIRECTIONS

Open the lid

Peel the foil seal to access the wipes

Pull out the central wipe

Thread the middle wipe through the opening of the lid

Re-place lid leaving the tissue through the top

Close lid to retain moisture

Lot. No:

Expiry: